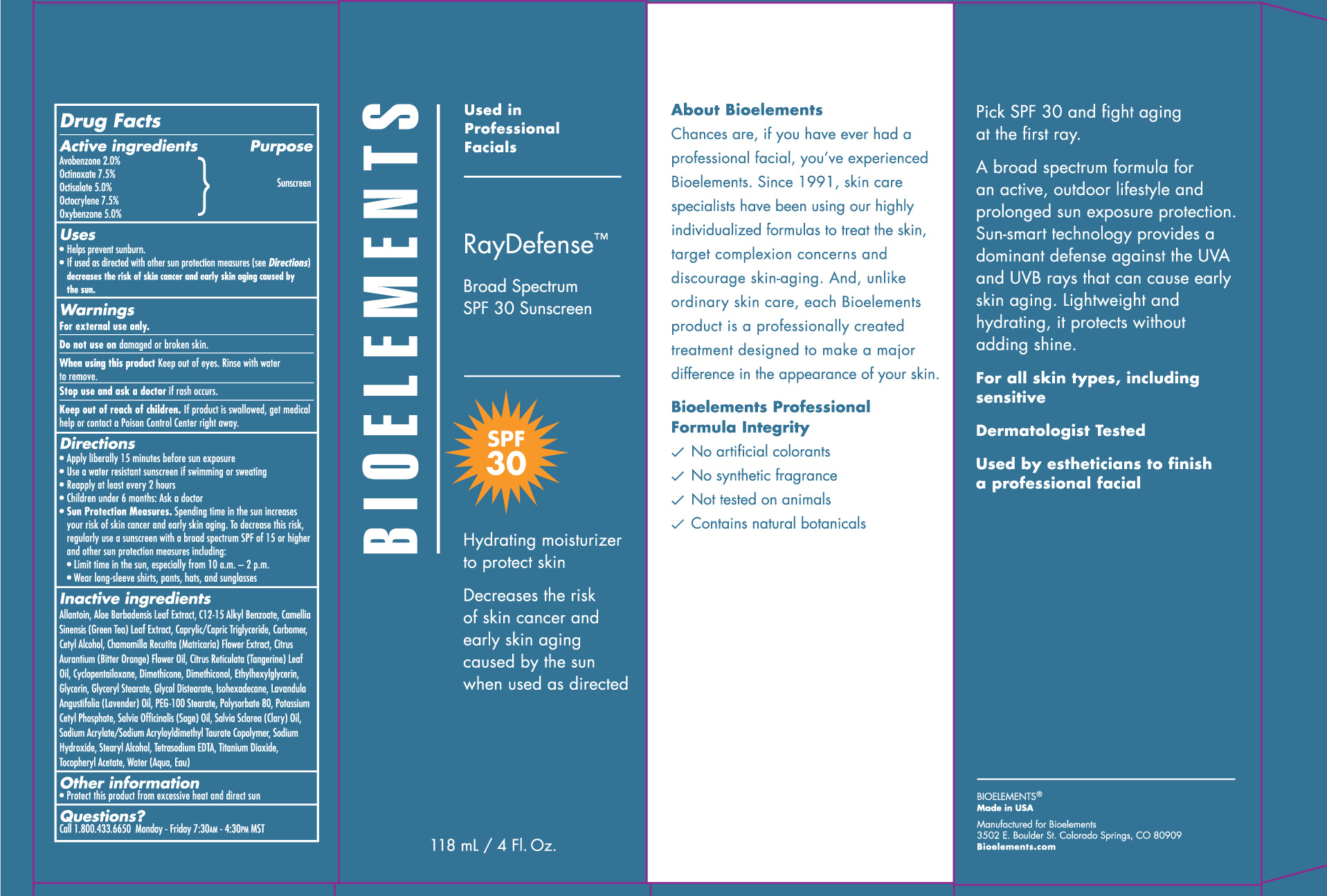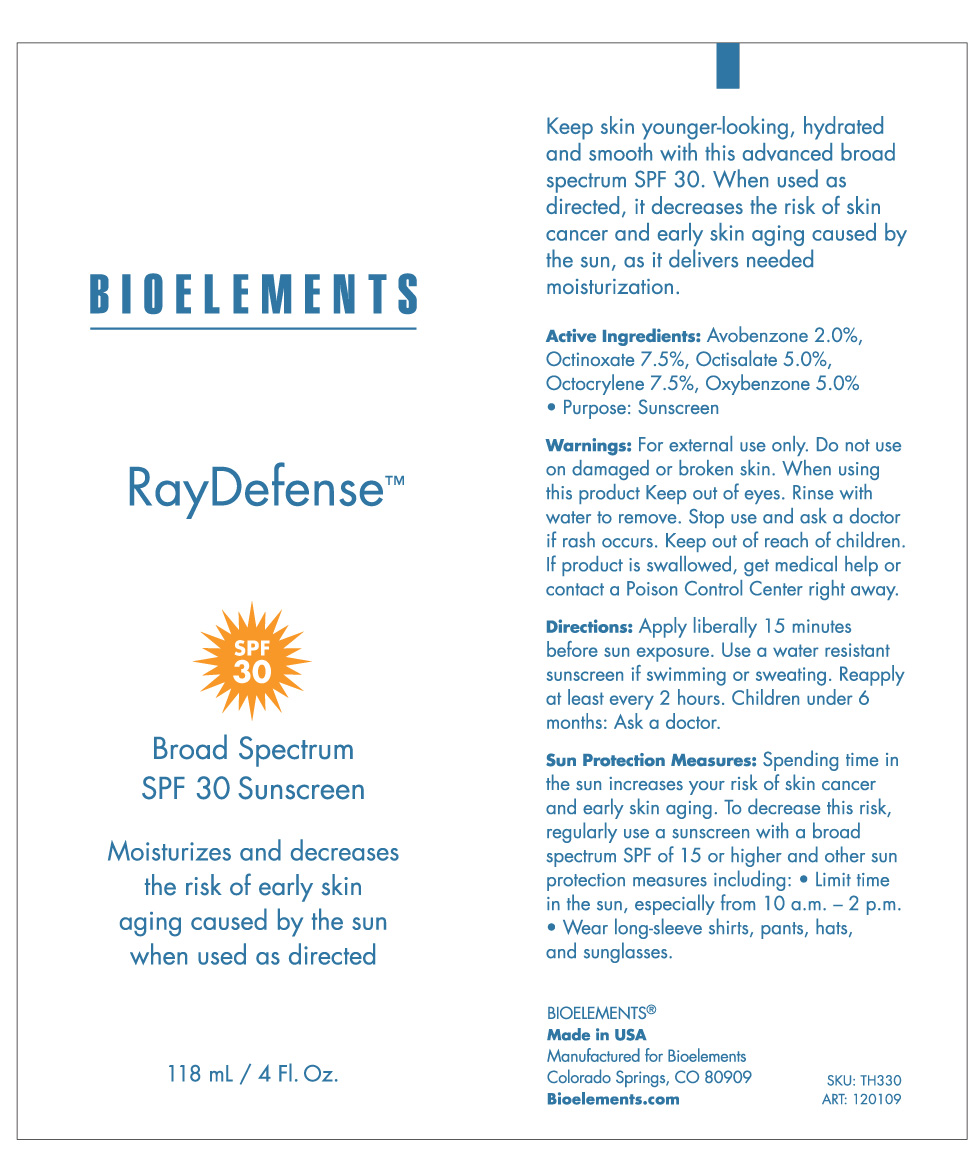 DRUG LABEL: Ray Defense
NDC: 49825-121 | Form: LIQUID
Manufacturer: Bioelements, Inc. 
Category: otc | Type: HUMAN OTC DRUG LABEL
Date: 20120329

ACTIVE INGREDIENTS: AVOBENZONE 2.0 mL/100 mL; OCTINOXATE 7.5 mL/100 mL; OCTISALATE 5.0 mL/100 mL; OCTOCRYLENE 7.5 mL/100 mL; OXYBENZONE 5.0 mL/100 mL
INACTIVE INGREDIENTS: ALLANTOIN; ALOE VERA LEAF; ALKYL (C12-15) BENZOATE; GREEN TEA LEAF; MEDIUM-CHAIN TRIGLYCERIDES; CETYL ALCOHOL; CHAMOMILE; CITRUS AURANTIUM FLOWER OIL; CITRUS RETICULATA LEAF OIL; CYCLOMETHICONE 5; DIMETHICONE; DIMETHICONOL (41 MPA.S); ETHYLHEXYLGLYCERIN; GLYCERIN; GLYCERYL MONOSTEARATE; GLYCOL DISTEARATE; ISOHEXADECANE; LAVENDER OIL; PEG-100 STEARATE; POLYSORBATE 80; POTASSIUM CETYL PHOSPHATE; SAGE OIL; CLARY SAGE OIL; SODIUM ACRYLATE/SODIUM ACRYLOYLDIMETHYLTAURATE COPOLYMER (4000000 MW); SODIUM HYDROXIDE; STEARYL ALCOHOL; EDETATE SODIUM; TITANIUM DIOXIDE; WATER

Ray Defense SPF 30

Active ingredients Purpose

Avobenzone 2.0 % Sunscreen

Octinoxate 7.5 % Sunscreen

Octisalate 5.0 % Sunscreen

Octocrylene 7.5 % Sunscreen

Oxybenzone 5.0% Sunscreen

Uses

Helps prevent sunburn

If used as directed with other sun protection measure (see Direction) decreases the risk of skin cancer and early skin aging caused by the sun.

Keep out of reach of children. If swallowed, get medical help or contact a Poison Control Center right away.

Stop use and ask a doctor if rash occurs

Warnings

For external Use only
Do not use on broken skin.
When using this product keep out of eyes. Rinse with water to remove.

Directions

Apply liberally 15 minutes before sun exposure

Use a water resistant sunscreen if swimming or sweating

Reapply at least every 2 hours

children under 6 months: Ask a doctor

Sun Protection Measures. Spending time in the sun increases your risk of skin cancer and early skin aging.To decrease this risk, regularly use a sunscreen with a broad spectrum SPF of 15 or higher and other sun protection measures including:

limit time in the sun, especially from 10 a.m. - 2 p.m.

Wear long-sleeve shirts, pants, hats, and sunglasses

Inactive Ingredients

Allantoin, Aloe Barbadensis Leaf Extract, C12-15 Alkyl Benzoate, Camellia Sinensis (Green Tea) Leaf Extract, Caprylic/Capric Triglyceride, Carbomer, Cetyl alcohol, Chamomilla Recutita (Matricaria) Flower Extract, Citrus Aurantium (Bitter Orange) Flower Oil, Citrus Reticulata (Tangerine) Leaf Oil, Cyclopentasiloxane, Dimethicone, Dimethiconol, Ehtylhexylglycerin, Glycerin, Glyceryl Stearate, Glycol Distearate, Isohexadecane, Lavandula Angustifolia (Lavender) Oil, PEG-100 Stearate, Polysorbate 80, Potassium Cetyl Phophate, Salvia Officinalis (Sage) Oil, Salvea Sclarea (Clary Oil), Sodium Acrylate/Sodium Acryloyldimethyl Taurate Copolymer, Sodium Hydroxide, Stearyl Alcohol, Tetrasodium EDTA,Titanium Dioxide, Tocopheryl Acetate, Water (Aqua, Eau)

PACKAGE LABEL

Bioelements

Ray Defense SPF 30
Broad Spectrum SPF 30 Sunscreen
Moisturizes and decreases the risk of early skin aging caused by the sun when used as directed.
118 mL / 4 Fl.Oz.